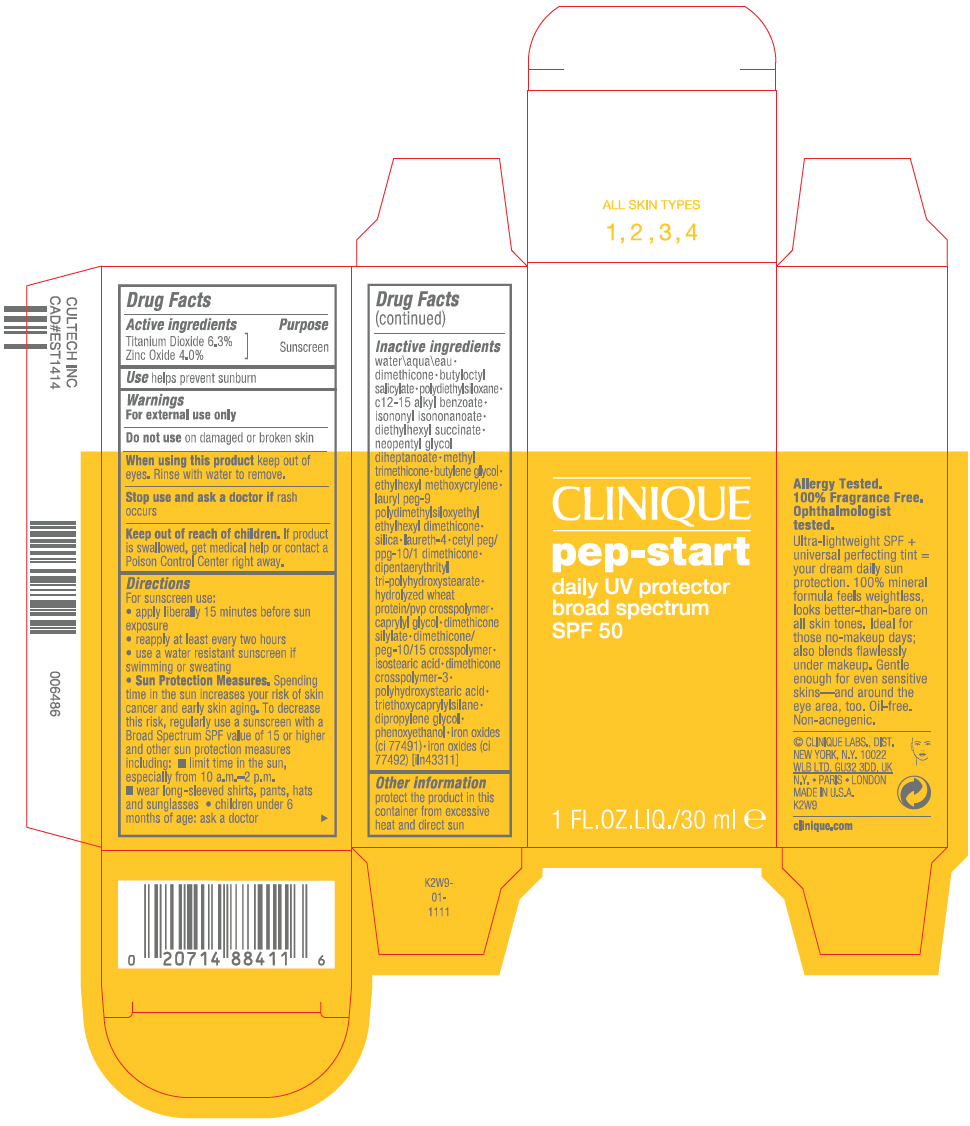 DRUG LABEL: PEP-STAR DAILY UV PROTECTOR BROAD SPECTRUM SPF 50
NDC: 49527-073 | Form: LOTION
Manufacturer: CLINIQUE LABORATORIES LLC
Category: otc | Type: HUMAN OTC DRUG LABEL
Date: 20231013

ACTIVE INGREDIENTS: TITANIUM DIOXIDE 63 mg/1 mL; ZINC OXIDE 40 mg/1 mL
INACTIVE INGREDIENTS: WATER; DIMETHICONE; BUTYLOCTYL SALICYLATE; ALKYL (C12-15) BENZOATE; ISONONYL ISONONANOATE; DIETHYLHEXYL SUCCINATE; NEOPENTYL GLYCOL DIHEPTANOATE; METHYL TRIMETHICONE; BUTYLENE GLYCOL; ETHYLHEXYL METHOXYCRYLENE; SILICON DIOXIDE; LAURETH-4; DIPENTAERYTHRITYL TRI-POLYHYDROXYSTEARATE; CAPRYLYL GLYCOL; ISOSTEARIC ACID; TRIETHOXYCAPRYLYLSILANE; DIPROPYLENE GLYCOL; PHENOXYETHANOL; FERRIC OXIDE RED; FERRIC OXIDE YELLOW

PEP-START DAILY UV PROTECTOR BROAD SPECTRUM SPF 50

Drug Facts

Active ingredients

Titanium Dioxide 6.3%
Zinc Oxide 4.0%

Purpose

Sunscreen

Use

helps prevent sunburn

Warnings

For external use only

Do not use on damaged or broken skin

When using this product keep out of eyes. Rinse with water to remove.

Stop use and ask a doctor if rash occurs

Keep out of reach of children. If product is swallowed, get medical help or contact a Poison Control Center right away.

Directions

For sunscreen use:

- apply liberally 15 minutes before sun exposure
- reapply at least every two hours
- use a water resistant sunscreen if swimming or sweating
- Sun Protection Measures. Spending time in the sun increases your risk of skin cancer and early skin aging. To decrease this risk, regularly use a sunscreen with a Broad Spectrum SPF value of 15 or higher and other sun protection measures including:
  - limit time in the sun, especially from 10 a.m.–2 p.m.
  - wear long-sleeved shirts, pants, hats and sunglasses
- children under 6 months of age: ask a doctor

Inactive ingredients

water\aqua\eau • dimethicone • butyloctyl salicylate • polydiethylsiloxane • c12-15 alkyl benzoate • isononyl isononanoate • diethylhexyl succinate • neopentyl glycol diheptanoate • methyl trimethicone • butylene glycol • ethylhexyl methoxycrylene • lauryl peg-9 polydimethylsiloxyethyl ethylhexyl dimethicone • silica • laureth-4 • cetyl peg/ppg-10/1 dimethicone • dipentaerythrityl tri-polyhydroxystearate • hydrolyzed wheat protein/pvp crosspolymer • caprylyl glycol • dimethicone silylate • dimethicone/peg-10/15 crosspolymer • isostearic acid • dimethicone crosspolymer-3 • polyhydroxystearic acid • triethoxycaprylylsilane • dipropylene glycol • phenoxyethanol • iron oxides (ci 77491) • iron oxides (ci 77492) [iln43311]

Other information

protect the product in this container from excessive heat and direct sun

PRINCIPAL DISPLAY PANEL - 30 ml Bottle Carton

CLINIQUE

pep-start

daily UV protector
broad spectrum
SPF 50

1 FL.OZ.LIQ./30 ml e